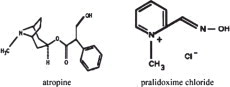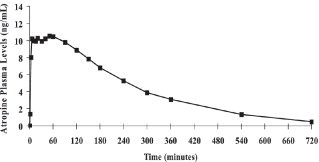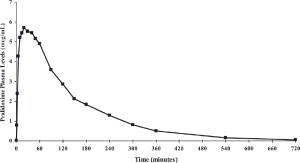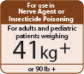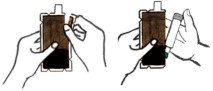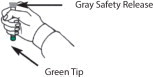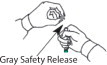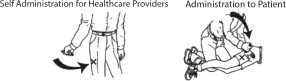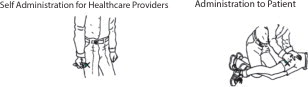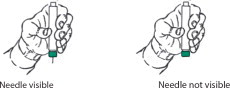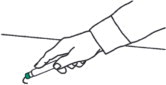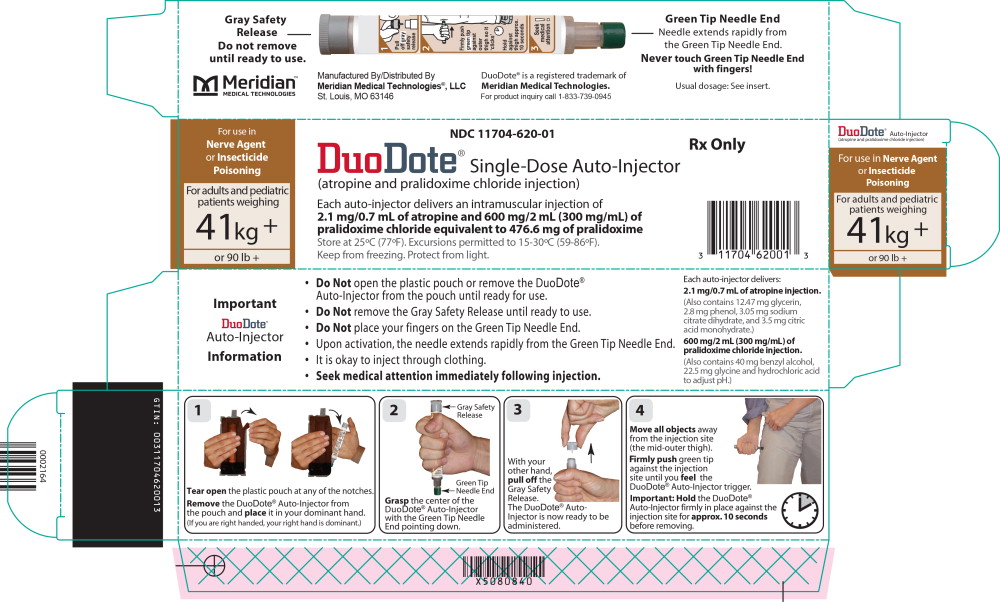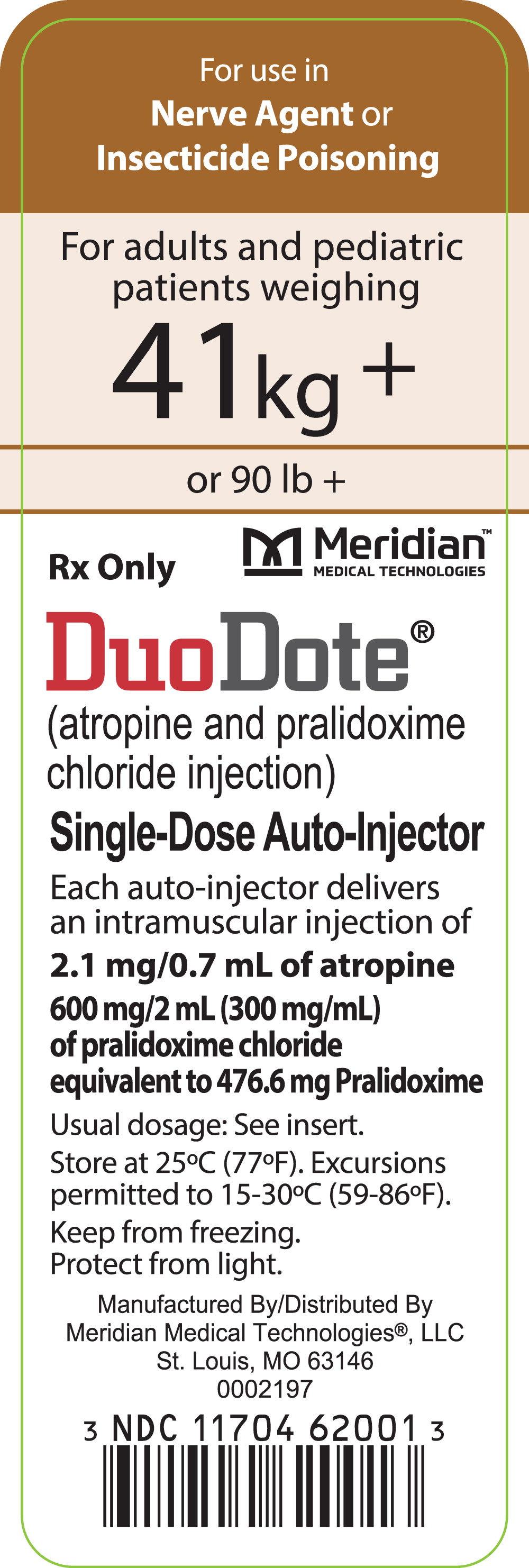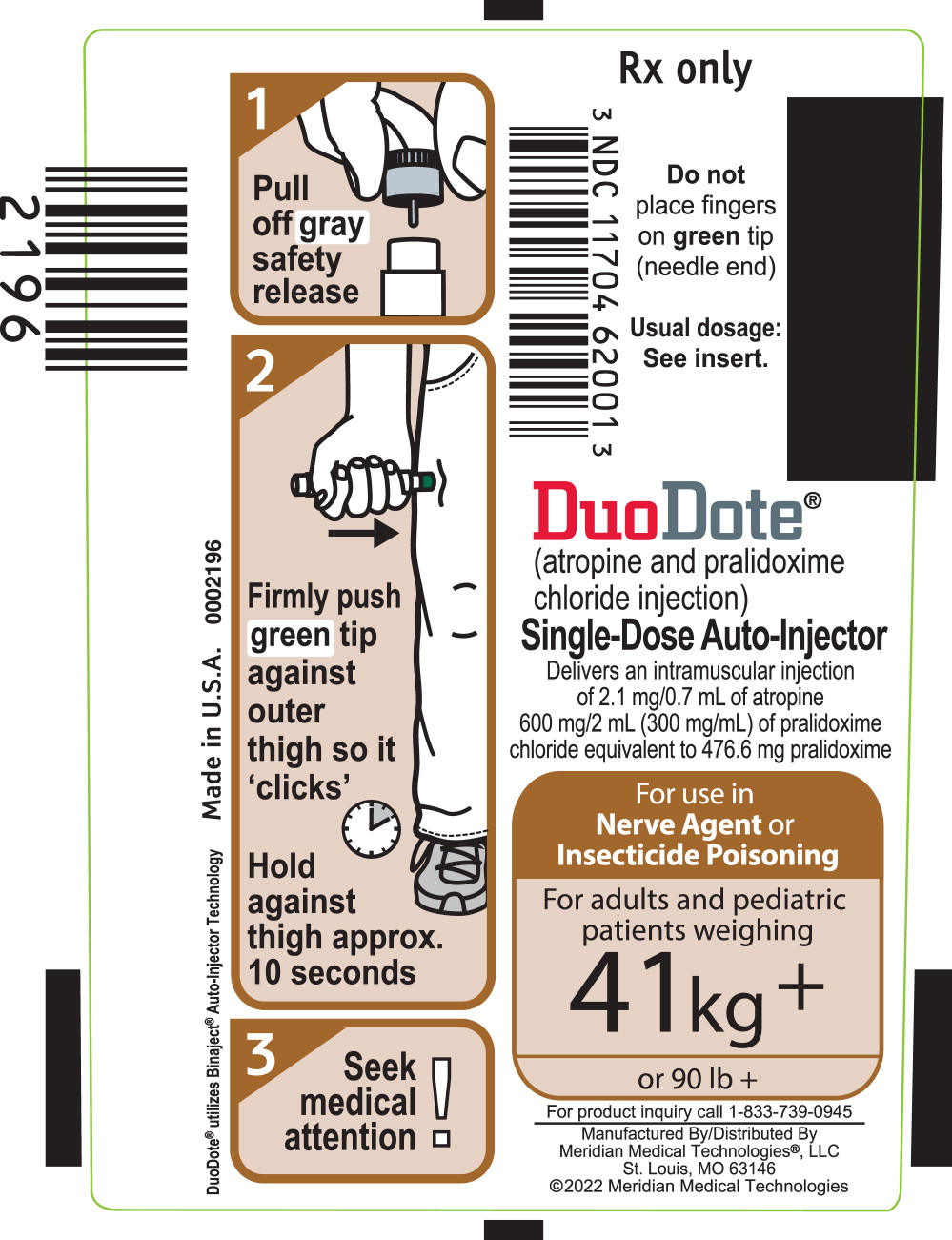 DRUG LABEL: DuoDote
NDC: 11704-620 | Form: KIT | Route: INTRAMUSCULAR
Manufacturer: Meridian Medical Technologies® LLC
Category: prescription | Type: HUMAN PRESCRIPTION DRUG LABEL
Date: 20220404

ACTIVE INGREDIENTS: atropine 2.1 mg/0.7 mL; pralidoxime chloride 600 mg/2 mL
INACTIVE INGREDIENTS: Glycerin; Citric Acid Monohydrate; Phenol; Water; Sodium Citrate; Nitrogen; Benzyl Alcohol; Glycine; Water; Hydrochloric Acid

HIGHLIGHTS OF PRESCRIBING INFORMATION

These highlights do not include all the information needed to use DUODOTE® safely and effectively. See full prescribing information for DUODOTE.
DUODOTE (atropine and pralidoxime chloride injection), for intramuscular use
Initial U.S. Approval: 2006

1 INDICATIONS AND USAGE

DuoDote, a combination of atropine, a cholinergic muscarinic antagonist, and pralidoxime chloride, a cholinesterase reactivator, is indicated for the treatment of poisoning by organophosphorus nerve agents as well as organophosphorus insecticides in adults and pediatric patients weighing more than 41 kg (90 pounds). (1)

2 DOSAGE AND ADMINISTRATION

- DuoDote is intended as an initial treatment as soon as symptoms appear; definitive medical care should be sought immediately. (2.1)
- Dosage for Mild Symptoms: If the patient experiences two or more mild symptoms, administer one injection intramuscularly into the mid-lateral thigh. If, at any time after the first dose, the patient develops any of the severe symptoms, administer two additional injections intramuscularly in rapid succession. (2.2)
- Dosage for Severe Symptoms: If a patient has any of the severe symptoms, immediately administer three injections intramuscularly into the patient's mid-lateral thigh in rapid succession. (2.2)

3 DOSAGE FORMS AND STRENGTHS

Each single-dose DuoDote autoinjector contains atropine (2.1 mg/0.7 mL) plus pralidoxime chloride (600 mg/2 mL). (3)

4 CONTRAINDICATIONS

None. (4)

5 WARNINGS AND PRECAUTIONS

- Cardiovascular (CV) Risks: Tachycardia, palpitations, premature ventricular contractions, flutter, fibrillation, etc. Use caution in patients with known CV disease or conduction problems. (5.1)
- Heat Injury: May inhibit sweating and lead to hyperthermia; avoid excessive exercising and heat exposure. (5.2)
- Acute Glaucoma: May precipitate in susceptible individuals. (5.3)
- Urinary Retention: Administer with caution in patient with bladder outflow obstruction. (5.4)
- Pyloric Stenosis: May convert into complete obstruction. (5.5)
- Exacerbation of Chronic Lung Disease: Atropine may cause inspissation of bronchial secretions and formation of dangerous viscid plugs in individuals with chronic lung disease; monitor respiratory status. (5.6)

6 ADVERSE REACTIONS

Common adverse reactions of atropine include dryness of mouth, blurred vision, dry eyes, photophobia, confusion, headache, and dizziness among others. (6.1) The common adverse reactions of pralidoxime chloride include changes in vision, dizziness, headache, drowsiness, nausea, tachycardia, increased blood pressure, muscular weakness, dry mouth, emesis, rash, dry skin, hyperventilation, decreased renal function, excitement, manic behavior, and transient elevation of liver enzymes and creatine phosphokinase. (6.2)

To report SUSPECTED ADVERSE REACTIONS, contact Meridian Medical Technologies®, LLC at 1-833-739-0945 or FDA at 1-800-FDA-1088 or www.fda.gov/medwatch.

7 DRUG INTERACTIONS

- Succinylcholine and Mivacurium: Accelerated reversal of neuromuscular blocking effects may occur; monitor with concomitant administration. (7.1)

8 USE IN SPECIFIC POPULATIONS

- Geriatric patients may be more susceptible to the effects of atropine. (8.5)

FULL PRESCRIBING INFORMATION

1 INDICATIONS AND USAGE

DuoDote is indicated for the treatment of poisoning by organophosphorus nerve agents as well as organophosphorus insecticides in adults and pediatric patients weighing more than 41 kg (90 pounds).

2 DOSAGE AND ADMINISTRATION

2.1 Important Administration Information

- Three (3) single-dose DuoDote autoinjectors should be available for use in each patient (including healthcare providers) at risk for organophosphorus poisoning; one (1) for mild symptoms plus two (2) more for severe symptoms [see Dosage and Administration (2.2)]. Note that individuals may not have all symptoms included under the mild or severe symptom category.
- Only administer DuoDote to patients experiencing symptoms of organophosphorus poisoning in a situation where exposure is known or suspected. The DuoDote autoinjector is intended as an initial treatment of the symptoms of organophosphorus nerve agent or insecticide poisonings as soon as symptoms appear; definitive medical care should be sought immediately.
- The DuoDote autoinjector should be administered by healthcare providers who have had adequate training in the recognition and treatment of nerve agent or insecticide intoxication.
- Close supervision of all treated patients is indicated for at least 48 to 72 hours.
- Parenteral drug products should be inspected visually for particulate matter and discoloration prior to administration, whenever solution and container permit [see Dosage Forms and Strengths (3)].

2.2 Dosage Information

Dosage for Mild Symptoms in Adults and Pediatric Patients Weighing More Than 41 kg (90 Pounds)

First Dose: If the patient experiences two or more mild symptoms of nerve agent or insecticide exposure listed in Table 1, administer one (1) single-dose DuoDote injection intramuscularly into the mid-lateral thigh.

Additional Doses: If, at any time after the first dose, the patient develops any of the severe symptoms listed in Table 1, administer two (2) additional single-dose DuoDote injections intramuscularly in rapid succession.

Wait 10 to 15 minutes for DuoDote to take effect. If, after 10 to 15 minutes, the patient does not develop any of the severe symptoms listed in Table 1, no additional DuoDote injections are recommended.

Dosage for Severe Symptoms in Adults and Pediatric Patients Weighing More Than 41 kg (90 Pounds)

If a patient has any of the severe symptoms listed in Table 1, immediately administer three (3) single-dose DuoDote injections intramuscularly into the patient's mid-lateral thigh in rapid succession.

Table 1. Common Symptoms of Organophosphorus Exposure
Mild Symptoms | Severe Symptoms
- Blurred vision, miosis - Excessive, unexplained teary eyes - Excessive, unexplained runny nose - Increased salivation such as sudden drooling - Chest tightness or difficulty breathing - Tremors throughout the body or muscular twitching - Nausea and/or vomiting - Unexplained wheezing, coughing or increased airway secretions - Acute onset of stomach cramps - Tachycardia or bradycardia | - Strange or confused behavior - Severe difficulty breathing or copious secretions from lungs/airway - Severe muscular twitching and general weakness - Involuntary urination and defecation - Convulsions - Unconsciousness

2.3 Administration Instructions

*Do Not Remove Gray Safety Release until ready to use.

*Never touch the Green Tip (Needle End)!

1) Tear open the plastic pouch at any of the notches. Remove the DuoDote autoinjector from the pouch.
2) Place the DuoDote autoinjector in your dominant hand. (If you are right-handed, your right hand is dominant.) Firmly grasp the center of the DuoDote autoinjector with the Green Tip (needle end) pointing down.
3) With your other hand, pull off the Gray Safety Release. DuoDote is now ready to be administered.
4) The injection site is the mid-lateral thigh area. The DuoDote autoinjector can inject through clothing. However, make sure pockets at the injection site are empty. People who may not have a lot of fat at the injection site should also be injected in the mid-lateral thigh, but before giving the injection, bunch up the thigh to provide a thicker area for injection.
5) Firmly push the Green Tip straight down (a 90° angle) against the mid-lateral thigh. Continue to firmly push until you feel the DuoDote autoinjector trigger. After the autoinjector triggers, hold the DuoDote autoinjector firmly in place against the injection site for approximately 10 seconds.
6) Remove the DuoDote autoinjector from the thigh and look at Green Tip. If the needle is visible, the drug has been administered. If the needle is not visible, check to be sure the Gray Safety Release has been removed, and then repeat above steps beginning with Step 4, but push harder in Step 5.
7) After the drug has been administered, push the needle against a hard surface to bend the needle back against the DuoDote autoinjector.
8) Put the used DuoDote autoinjector back into the plastic pouch, if available. Leave used DuoDote autoinjector(s) with the patient to allow other medical personnel to see the number of DuoDote autoinjector(s) administered.
9) Immediately move yourself and the patient away from the contaminated area and seek definitive medical care for the patient.

3 DOSAGE FORMS AND STRENGTHS

Each single-dose DuoDote autoinjector contains the following in two separate chambers:

- front chamber (visible): a clear, colorless to yellow, sterile solution of atropine (2.1 mg/0.7 mL)
- back chamber (not visible): a clear, colorless to yellow, sterile solution of pralidoxime chloride (600 mg/2 mL) equivalent to pralidoxime (476.6 mg/2 mL)

When activated, DuoDote sequentially administers both drugs intramuscularly through a single needle in one injection.

4 CONTRAINDICATIONS

None.

5 WARNINGS AND PRECAUTIONS

5.1 Cardiovascular Risks

Cardiovascular adverse reactions reported in the literature for atropine include, but are not limited to, sinus tachycardia, palpitations, premature ventricular contractions, atrial flutter, atrial fibrillation, ventricular flutter, ventricular fibrillation, cardiac syncope, asystole, and myocardial infarction. In patients with a recent myocardial infarction and/or severe coronary artery disease, there is a possibility that atropine-induced tachycardia may cause ischemia, extend or initiate myocardial infarcts, and stimulate ventricular ectopy and fibrillation. DuoDote should be used with caution in patients with known cardiovascular disease or cardiac conduction problems.

5.2 Heat Injury

Atropine may inhibit sweating which, in a warm environment or with excessive exercise, can lead to hyperthermia and heat injury. To the extent feasible, avoid excessive exercise and heat exposure [see Overdosage (10.2)].

5.3 Acute Glaucoma

Atropine should be administered with caution in patients at risk for acute glaucoma.

5.4 Urinary Retention

Atropine should be administered with caution in patients with clinically significant bladder outflow obstruction because of the risk of urinary retention.

5.5 Pyloric Stenosis

Atropine should be administered with caution in patients with partial pyloric stenosis because of the risk of complete pyloric obstruction.

5.6 Exacerbation of Chronic Lung Disease

Atropine may cause inspissation of bronchial secretions and formation of dangerous viscid plugs in individuals with chronic lung disease. Respiratory status should be monitored in individuals with chronic lung disease following administration of DuoDote.

6 ADVERSE REACTIONS

The following serious adverse reactions are described elsewhere in the labeling:

- Cardiovascular Risks [see Warnings and Precautions (5.1)]
- Heat Injury [see Warnings and Precautions (5.2)]
- Acute Glaucoma [see Warnings and Precautions (5.3)]
- Urinary Retention [see Warnings and Precautions (5.4)]
- Pyloric Stenosis [see Warnings and Precautions (5.5)]
- Exacerbation of Chronic Lung Disease [see Warnings and Precautions (5.6)]

The following adverse reactions associated with the use of atropine and pralidoxime chloride were identified in the literature. Because these reactions are reported voluntarily from a population of uncertain size, it is not always possible to reliably estimate their frequency or establish a causal relationship to drug exposure.

6.1 Atropine

Because DuoDote contains pralidoxime chloride, which may potentiate the effect of atropine, signs of atropinization may occur earlier than might be expected when atropine is used alone.

Common adverse reactions of atropine can be attributed to its antimuscarinic action. These include dryness of the mouth, blurred vision, dry eyes, photophobia, confusion, headache, dizziness, tachycardia, palpitations, flushing, urinary hesitancy or retention, constipation, abdominal pain, abdominal distention, nausea and vomiting, loss of libido, and impotence. Anhidrosis may produce heat intolerance and impairment of temperature regulation in a hot environment. Dysphagia, paralytic ileus, acute angle closure glaucoma, maculopapular rash, petechial rash, and scarletiniform rash have also been reported. Adverse cardiac reactions, including arrhythmias and myocardial infarction, have been reported with atropine [see Warnings and Precautions (5.1) and Clinical Pharmacology (12.2)].

Larger doses of atropine may produce central nervous system effects such as restlessness, tremor, fatigue, locomotor difficulties, delirium, and hallucinations [see Overdosage (10.1)].

Hypersensitivity reactions will occasionally occur, are usually seen as skin rashes, and may progress to exfoliation. Anaphylactic reaction and laryngospasm are rare.

6.2 Pralidoxime Chloride

Pralidoxime can cause blurred vision, diplopia and impaired accommodation, dizziness, headache, drowsiness, nausea, tachycardia, increased systolic and diastolic blood pressure [see Clinical Pharmacology (12.2)], muscular weakness, dry mouth, emesis, rash, dry skin, hyperventilation, decreased renal function, and decreased sweating when given parenterally to normal adult volunteers who have not been exposed to anticholinesterase poisons.

In several cases of organophosphorus poisoning, excitement and manic behavior have occurred immediately following recovery of consciousness, in either the presence or absence of pralidoxime administration. However, similar behavior has not been reported in subjects given pralidoxime in the absence of organophosphorus poisoning.

Elevations in AST and/or ALT enzyme levels were observed in 1 of 6 normal adult volunteers given 1200 mg of pralidoxime intramuscularly, and in 4 of 6 adult volunteers given 1800 mg intramuscularly. Levels returned to normal in about two weeks. Transient elevations in creatine kinase were observed in all normal volunteers given the drug.

6.3 Injection Site

Muscle tightness and pain may occur at the injection site.

6.4 Inadvertent Injection

In cases where DuoDote is inadvertently administered to people who are not poisoned with nerve agent or organophosphorus insecticide, the following effects on their ability to function normally may occur.

Atropine 2 mg IM, roughly the equivalent of one DuoDote autoinjector, when given to healthy male volunteers, is associated with minimal effects on visual, motor, and mental functions, though unsteadiness walking and difficulty concentrating may occur. Atropine reduces body sweating and increases body temperature, particularly with exercise and under hot conditions.
Atropine 4 mg IM, roughly the equivalent of two DuoDote autoinjectors, when given to healthy male volunteers, is associated with impaired visual acuity, visual near point accommodation, logical reasoning, digital recall, learning, and cognitive reaction time. Ability to read is reduced or lost. Subjects are unsteady and need to concentrate on walking. These effects begin about 15 minutes to one hour or more post-dose.
Atropine 6 mg IM, roughly the equivalent of three DuoDote autoinjectors, when given to healthy male volunteers, is associated with the effects described above plus additional central effects including poor coordination, poor attention span, and visual hallucinations (colored flashes) in many subjects. Frank visual hallucinations, auditory hallucinations, disorientation, and ataxia occur in some subjects. Skilled and labor-intense tasks are performed more slowly and less efficiently. Decision making takes longer and is sometimes impaired.

It is unclear if the above data, obtained from studies of healthy adult subjects, can be extrapolated to other populations. In the elderly and patients with co-morbid conditions, the effects of ≥2 mg atropine on the ability to see, walk, and think properly are unstudied; effects may be greater in susceptible populations.

Patients who are mistakenly injected with DuoDote should avoid potentially dangerous overheating, avoid vigorous physical activity, and seek medical attention as soon as feasible.

7 DRUG INTERACTIONS

7.1 Succinylcholine and Mivacurium

Since pralidoxime in DuoDote reactivates cholinesterases and succinylcholine and mivacurium are metabolized by cholinesterases, patients with organophosphorus nerve agent or organophosphorus insecticide poisoning who have received DuoDote may exhibit accelerated reversal of the neuromuscular blocking effects of succinylcholine and mivacurium (relative to poisoned patients who have not received pralidoxime). Monitor for neuromuscular effects with concomitant administration.

8 USE IN SPECIFIC POPULATIONS

8.1 Pregnancy

Risk Summary
Atropine readily crosses the placental barrier and enters fetal circulation. There are no adequate data on the developmental risk associated with the use of atropine, pralidoxime, or the combination in pregnant women. Adequate animal reproduction studies have not been conducted with atropine, pralidoxime, or the combination. In the U.S. general population, the estimated background risk of major birth defects and miscarriage in clinically recognized pregnancies is 2-4% and 15-20%, respectively.

8.2 Lactation

Risk Summary
Atropine has been reported to be excreted in human milk. It is not known whether pralidoxime is excreted in human milk. There are no data on the effects of atropine or pralidoxime on the breastfed infant or the effects of the drugs on milk production. The developmental and health benefits of breastfeeding should be considered along with the mother's clinical need for DuoDote and any potential adverse effects on the breastfed infant from DuoDote or from the underlying maternal condition.

8.4 Pediatric Use

Safety and effectiveness of atropine in DuoDote in patients weighing more than 41 kg (90 pounds) is supported by published literature. Safety and effectiveness of pralidoxime chloride in DuoDote in patients more than 41 kg (90 pounds) is supported by data from pharmacokinetic studies in adults and experience in the pediatric population. Adverse events seen in pediatric patients treated with atropine are similar to those that occur in adult patients, although central nervous system complaints are often seen earlier and at lower doses [see Adverse Reactions (6.1)].

Safety and effectiveness of DuoDote in pediatric patients weighing less than or equal to 41 kg (90 pounds) have not been established.

8.5 Geriatric Use

Geriatric patients may be more susceptible to the effects of atropine [see Clinical Pharmacology (12.3)].

8.6 Renal Impairment

Pralidoxime chloride can cause decreased renal function [see Adverse Reactions (6.2)]. Patients with severe renal impairment may require less frequent doses after the initial dose.

8.7 Hepatic Impairment

Patients with severe hepatic impairment may require less frequent doses after the initial dose.

10 OVERDOSAGE

10.1 Symptoms

Atropine
Manifestations of atropine overdose are dose-related and include flushing, dry skin and mucous membranes, tachycardia, widely dilated pupils that are poorly responsive to light, blurred vision, and fever (which can sometimes be dangerously elevated). Locomotor difficulties, disorientation, hallucinations, delirium, confusion, agitation, coma, and central depression can occur and may last 48 hours or longer. In instances of severe atropine intoxication, respiratory depression, coma, circulatory collapse, and death may occur.

Pralidoxime
It may be difficult to differentiate adverse events caused by pralidoxime from those caused by organophosphorus poisoning. Symptoms of pralidoxime overdose may include dizziness, blurred vision, diplopia, headache, impaired accommodation, nausea, and tachycardia. Transient hypertension caused by pralidoxime may last several hours.

10.2 Treatment

For atropine overdose, supportive treatment should be administered. If respiration is depressed, artificial respiration with oxygen is necessary. Ice bags, a hypothermia blanket, or other methods of cooling may be required to reduce atropine-induced fever, especially in pediatric patients. Catheterization may be necessary if urinary retention occurs. Since atropine elimination largely takes place through the kidney, urinary output must be maintained and increased if possible; intravenous fluids may be indicated. Because of atropine-induced photophobia, the room should be darkened.

A benzodiazepine may be needed to control marked excitement and convulsions. However, large doses for sedation should be avoided because the central nervous system depressant effect may coincide with the depressant effect occurring late in severe atropine poisoning. Barbiturates are potentiated by the anticholinesterases; therefore, barbiturates should be used cautiously in the treatment of convulsions. Central nervous system stimulants are not recommended.

11 DESCRIPTION

Each prefilled DuoDote autoinjector provides a single intramuscular dose of atropine, a cholinergic muscarinic antagonist, and pralidoxime chloride, a cholinesterase reactivator, in a self-contained unit, specifically designed for administration by emergency medical services personnel.

When activated, each single-dose DuoDote autoinjector delivers the following:

- 2.1 mg of atropine in 0.7 mL of sterile, pyrogen-free solution containing 12.47 mg glycerin, not more than 2.8 mg phenol, 3.05 mg sodium citrate dihydrate, 3.5 mg citric acid monohydrate, and Water for Injection. The pH range is 4.0 – 5.0.
- 600 mg of pralidoxime chloride equivalent to 476.6 mg of pralidoxime in 2 mL of sterile, pyrogen-free solution containing 40 mg benzyl alcohol, 22.5 mg glycine, and Water for Injection. The pH is adjusted with hydrochloric acid. The pH range is 2.0 to 3.0.

Atropine occurs as white crystals, usually needle-like, or as a white, crystalline powder. It is slightly soluble in water with a molecular weight of 289.38. Atropine, a naturally occurring belladonna alkaloid, is a racemic mixture of equal parts of d- and l-hyoscyamine, with activity due almost entirely to the levo isomer of the drug.

Chemically, atropine is designated as 1αH,5αH-Tropan-3α-ol(±)-tropate. Its empirical formula is C17H23NO3 and its structural formula is as follows:

Pralidoxime chloride is an odorless, white to pale-yellow crystalline powder, freely soluble in water, with a molecular weight of 172.61. Chemically, pralidoxime chloride is designated as 2-formyl-l-methylpyridinium chloride oxime. Its empirical formula is C7H9ClN2O and its structural formula is indicated above.

12 CLINICAL PHARMACOLOGY

12.1 Mechanism of Action

Atropine
Atropine competitively blocks the effects of acetylcholine, including excess acetylcholine due to organophosphorus poisoning, at muscarinic cholinergic receptors on smooth muscle, cardiac muscle, secretory gland cells, and in peripheral autonomic ganglia and the central nervous system.

Pralidoxime
Pralidoxime reactivates acetylcholinesterase which has been inactivated by phosphorylation due to an organophosphorus nerve agent or insecticide. However, pralidoxime does not reactivate acetylcholinesterase inactivated by all organophosphorus nerve agents (e.g., soman). Pralidoxime cannot reactivate phosphorylated acetylcholinesterases that have undergone a further chemical reaction known as “aging.” Reactivated acetylcholinesterase hydrolyzes excess acetylcholine resulting from organophosphorus poisoning to help restore impaired cholinergic neural function. Reactivation is clinically important because only a small proportion of active acetylcholinesterase is needed to maintain vital functions.

12.2 Pharmacodynamics

Atropine
Atropine reduces secretions in the mouth and respiratory passages, relieves airway constriction, and may reduce centrally-mediated respiratory paralysis. In severe organophosphorus poisoning, a fully atropinized patient may develop or continue to have respiratory failure and may require artificial respiration and suctioning of airway secretions. Atropine may cause thickening of secretions.

Atropine-induced parasympathetic inhibition may be preceded by a transient phase of stimulation, especially on the heart where small doses first slow the rate before characteristic tachycardia develops due to paralysis of vagal control. Atropine increases heart rate and reduces atrioventricular conduction time. Adequate atropine doses can prevent or abolish bradycardia or asystole produced by organophosphorus nerve agents.

Atropine may decrease the degree of partial heart block which can occur after organophosphorus poisoning. In some patients with complete heart block, atropine may accelerate the idioventricular rate; in others, the rate is stabilized. In some patients with conduction defects, atropine may cause paradoxical atrioventricular (A-V) block and nodal rhythm.

Atropine will not act on the neuromuscular junction and has no effect on muscle paralysis or weakness, fasciculations or tremors; pralidoxime is intended to treat these symptoms.

Systemic doses of atropine slightly raise systolic and lower diastolic pressures and can produce significant postural hypotension. Such doses also slightly increase cardiac output and decrease central venous pressure. Atropine can dilate cutaneous blood vessels, particularly the “blush” area (atropine flush), and may inhibit sweating, thereby causing hyperthermia, particularly in a warm environment or with exercise [see Warnings and Precautions (5.2)].

Pralidoxime Chloride
Pralidoxime chloride has its most critical effect in relieving respiratory muscle paralysis. Because pralidoxime is less effective in relieving depression of the respiratory center, atropine is always required concomitantly to block the effect of accumulated acetylcholine at this site. Pralidoxime has a minor role in relieving muscarinic signs and symptoms, such as salivation or bronchospasm.

DuoDote temporarily increases blood pressure, a known effect of pralidoxime. In a study of 24 healthy young adults administered a single dose of atropine and pralidoxime autoinjector intramuscularly (approximately 9 mg/kg pralidoxime chloride), diastolic blood pressure increased from baseline by 11 ± 14 mm Hg (mean ± SD), and systolic blood pressure increased by 16 ± 19 mm Hg, at 15 minutes post-dose. Blood pressures remained elevated at these approximate levels through one hour post-dose, began to decrease at two hours post-dose and were near pre-dose baseline at four hours post-dose.

12.3 Pharmacokinetics

Atropine:
Atropine is well absorbed after intramuscular administration. Single dose DuoDote pharmacokinetic data for atropine are shown in Figure 1. The intramuscular injection site was the antero-lateral thigh.

Mean atropine plasma concentrations shown in Figure 1 indicate a plateau beginning at about 5 minutes post-dose and extending through 60 minutes post-dose.

Figure 1. Mean Atropine Plasma Concentrations After a Single DuoDote Intramuscular Injection, Which Delivers 2.1 mg of Atropine Base and 600 mg Pralidoxime Chloride, N=24 Healthy Adult Subjects [Men (n=12), Women (n=12)].

Pralidoxime Chloride:
Pralidoxime chloride is rapidly absorbed after intramuscular injection. DuoDote single dose pharmacokinetic data for pralidoxime chloride 600 mg are provided in Figure 2.

Figure 2. Mean Pralidoxime Plasma Concentrations After a Single DuoDote Intramuscular Injection, Which Delivers 2.1 mg of Atropine and 600 mg Pralidoxime Chloride, N=24 Healthy Adult Subjects.

The pharmacokinetic properties of the components of DuoDote are presented in Table 2.

Table 2. Pharmacokinetic Properties of the Components of DuoDote Following Intramuscular Administration in Healthy Subjects
Pharmacokinetics related to: | Atropine | Pralidoxime
Absorption
Cmax (mean ± standard deviation) | 13 ± 3 ng/mL | 7 ± 3 mcg/mL
Tmax (mean ± standard deviation) | 31 ± 30 minutes | 28 ± 15 minutes
Distribution
Protein binding | 14 to 22% to plasma proteins | Not appreciable bound to serum proteins
Elimination
T½ | 2.4 ± 0.3 hours | 2 ± 1 hours
Major route of excretion | Urinary | Urinary
Percentage of dose excreted in urine | 50 to 60% as unchanged drug. About 17 to 28% eliminated in the first 100 minutes. | 72 to 94% as unchanged drug. About 57 to 70% eliminated in the first 30 minutes, partly as metabolite.

Specific Populations

Renal and Hepatic Impairment
The pharmacokinetics of atropine or pralidoxime have not been evaluated in subjects with renal or hepatic impairment.

Gender
Atropine: DuoDote AUC0-inf and Cmax values for atropine are 15% higher in females than males. The half-life of atropine is approximately 20 minutes shorter in females than males.

Pralidoxime Chloride: A single DuoDote injection produced a mean Cmax for pralidoxime about 36% higher in females than males. Tmax is 23 minutes in females and 32 minutes in males. Pralidoxime half-life in males and females are 153 and 107 minutes, respectively.

Geriatric
Atropine: Half-life of intravenous atropine is 3.0 ± 0.9 hours in adults and 10.0 ± 7.3 hours in geriatric patients (65-75 years of age).

13 NONCLINICAL TOXICOLOGY

13.1 Carcinogenesis, Mutagenesis, Impairment of Fertility

Carcinogenesis
DuoDote is indicated for short-term emergency use only, and no adequate studies regarding the carcinogenic potential of atropine or pralidoxime chloride have been conducted.

Mutagenesis
Studies to assess the mutagenic potential of atropine or pralidoxime chloride have not been conducted.

Impairment of Fertility

Atropine:
In studies in which male rats were orally administered atropine (62.5 to 125 mg/kg) for one week prior to mating and throughout a 5-day mating period with untreated females, a dose-related decrease in fertility was observed. A no-effect dose for male reproductive toxicity was not established. The lowest dose tested was 290 times (on a mg/m^2 basis) the dose of atropine in a single application of DuoDote (2.1 mg).

Fertility studies of atropine in females have not been conducted.

Pralidoxime Chloride:
The effects of pralidoxime chloride on fertility have not been assessed.

16 HOW SUPPLIED/STORAGE AND HANDLING

Each single-dose DuoDote (atropine and pralidoxime chloride) autoinjector contains atropine (2.1 mg/0.7 mL; colorless to yellow solution, visible in front chamber) and pralidoxime chloride (600 mg/2 mL; colorless to yellow solution, not visible in rear chamber) and is available in a single unit carton, NDC-11704-620-01.

Each DuoDote autoinjector is supplied in a pouch that provides protection from light.

Store at 25ºC (77ºF); excursions permitted between 15ºC and 30ºC (between 59ºF and 86ºF) [See USP Controlled Room Temperature]. Not made with natural rubber latex. Keep from freezing. Protect from light.

17 PATIENT COUNSELING INFORMATION

Use by Healthcare Providers
DuoDote is intended for use by Healthcare Providers. See the illustrated Instruction Sheet for Healthcare Providers.

Seek Definitive Medical Care
If feasible and appropriate, advise patients that DuoDote is an initial emergency treatment, that they need additional care at a healthcare facility.

Avoid Overheating
If feasible and appropriate, advise the patient to avoid a hot environment and excessive physical activity since DuoDote can inhibit sweating which can lead to overheating and heat injury.

Manufactured by:
Meridian Medical Technologies®, LLC
St. Louis, MO 63146

INSTRUCTIONS FOR USE

Instruction Sheet for
Healthcare Providers

DuoDote is a single-dose autoinjector that should be administered by healthcare providers who have had adequate training in the recognition and treatment of nerve agent or insecticide intoxication.

Individuals should not rely solely upon atropine and pralidoxime to provide complete protection from chemical nerve agents and insecticide poisoning.

Primary protection against exposure to chemical nerve agents and insecticide poisoning is the wearing of protective garments including masks designed specifically for this use.

Evacuation and decontamination procedures should be undertaken as soon as possible. Medical personnel assisting evacuated victims of nerve agent poisoning should avoid contaminating themselves by exposure to the victim's clothing.

DuoDote is indicated for the treatment of poisoning by organophosphorus nerve agents as well as organophosphorus insecticides in adults and pediatric patients weighing more than 41 kg (90 pounds). DuoDote should only be administered to patients experiencing symptoms of organophosphorus poisoning in a situation where exposure is known or suspected. DuoDote should be administered as soon as symptoms of organophosphorus poisoning appear.

The number of DuoDote autoinjectors to administer to an individual is based on severity of symptoms. Common symptoms of organophosphorus exposure are listed below. Individuals may not have all symptoms:

Mild Symptoms | Severe Symptoms
- Blurred vision, miosis - Excessive, unexplained teary eyes - Excessive, unexplained runny nose - Increased salivation such as sudden drooling - Chest tightness or difficulty breathing - Tremors throughout the body or muscular twitching - Nausea and/or vomiting - Unexplained wheezing, coughing or increased airway secretions - Acute onset of stomach cramps - Tachycardia or bradycardia | - Strange or confused behavior - Severe difficulty breathing or copious secretions from lungs/airway - Severe muscular twitching and general weakness - Involuntary urination and defecation - Convulsions - Unconsciousness

Dosage for Mild Symptoms in Adults and Pediatric Patients Weighing More Than 41 kg (90 Pounds)
First Dose: Administer one (1) DuoDote injection into the mid-lateral thigh if the patient experiences two or more mild symptoms of nerve agent or insecticide exposure.

Trained healthcare providers with mild symptoms may self-administer a single-dose of DuoDote.

Wait 10 to 15 minutes for DuoDote to take effect. If, after 10 to 15 minutes, the patient does not develop any of the severe symptoms listed above, no additional DuoDote injections are recommended, but definitive medical care should ordinarily be sought immediately. For healthcare providers who have self-administered DuoDote, an individual decision will need to be made to determine their capacity to continue to provide emergency care.

Additional Doses: If, at any time after the first dose, the patient develops any of the severe symptoms listed above, administer two (2) additional DuoDote injections in rapid succession, and immediately seek definitive medical care.

Dosage for Severe Symptoms in Adults and Pediatric Patients Weighing More Than 41 kg (90 Pounds)
If a patient has any of the severe symptoms listed above, immediately administer three (3) DuoDote injections into the patient's mid-lateral thigh in rapid succession, and immediately seek definitive medical care.

Emergency care of the severely poisoned individual should include removal of oral and bronchial secretions, maintenance of a patent airway, supplemental oxygen, and, if necessary, artificial ventilation.

An anticonvulsant such as a benzodiazepine may be administered to treat convulsions if suspected in the unconscious individual. The effects of nerve agents and some insecticides can mask the motor signs of a seizure.

Close supervision of all severely poisoned patients is indicated for at least 48 to 72 hours.

Instructions for Use of the DuoDote Autoinjector
Do Not Remove Gray Safety Release until ready to use
Never touch the Green Tip (Needle End)!
Weight Guidelines
 | For use with adults and pediatric patients weighing more than 41 kg (90 lb). | For patients weighing less than or equal to 41 kg (90 lb) use the appropriate dose of:; - ATROPEN® or atropine from a vial - Pralidoxime chloride from a vial

1) Tear open the plastic pouch at any of the notches. Remove the DuoDote autoinjector from the pouch.
2) Place the DuoDote autoinjector in your dominant hand. (If you are right-handed, your right hand is dominant.) Firmly grasp the center of the DuoDote autoinjector with the Green Tip (needle end) pointing down.
3) With your other hand, pull off the Gray Safety Release. DuoDote is now ready to be administered.
4) The injection site is the mid-lateral thigh area. The DuoDote autoinjector can inject through clothing. However, make sure pockets at the injection site are empty.
  People who may not have a lot of fat at the injection site should also be injected in the mid-lateral thigh, but before giving the injection, bunch up the thigh to provide a thicker area of injection.
5) Firmly push the Green Tip straight down (at a 90° angle) against the mid-lateral thigh. Continue to firmly push until you feel the DuoDote autoinjector trigger.
  IMPORTANT: After the autoinjector triggers, hold the DuoDote autoinjector firmly in place against the injection site for approximately 10 seconds.
6) Remove the DuoDote autoinjector from the thigh and look at the Green Tip. If the needle is visible, the drug has been administered. If the needle is not visible, check to be sure the Gray Safety Release has been removed, and then repeat above steps beginning with Step 4, but push harder in Step 5.
7) After the drug has been administered, push the needle against a hard surface to bend the needle back against the DuoDote autoinjector.
8) Put the used DuoDote autoinjector back into the plastic pouch, if available. Leave used DuoDote autoinjector(s) with the patient to allow other medical personnel to see the number of DuoDote autoinjector(s) administered.
9) Immediately move yourself and the patient away from the contaminated area and seek definitive medical care for the patient.

DuoDote® is a registered trademark of:
Meridian Medical Technologies®, LLC
St. Louis, MO 63146
1-833-739-0945
© 2022 by Meridian Medical Technologies, LLC
Revised: 06/2022
0002165

Principal Display Panel - DuoDote Carton Label

For use in Nerve Agent
or Insecticide
Poisoning

For adults and pediatric
patients weighing
41 kg +
or 90 lb +

NDC 11704-620-01

Rx Only

DuoDote® Single-Dose Auto-Injector

(atropine and pralidoxime chloride injection)

Each auto-injector delivers an intramuscular injection of
2.1 mg/0.7 mL of atropine and 600 mg/2 mL (300 mg/mL) of
pralidoxime chloride equivalent to 476.6 mg of pralidoxime

Store at 25°C (77°F). Excursions permitted to 15-30°C (59-86°F).

Keep from freezing. Protect from light.

11704-62001

Principal Display Panel - DuoDote Pouch Label

For use in
Nerve Agent or
Insecticide Poisoning

For adults and pediatric
patients weighing
41 kg +
or 90 lb +

Rx Only

MERIDIAN
MEDICAL TECHNOLOGIES®

DuoDote®

(atropine and pralidoxime
chloride injection)

Single-Dose Auto-Injector

Each auto-injector delivers
an intramuscular injection of
2.1 mg/0.7 mL of atropine
600 mg/2 mL (300 mg/mL)
of pralidoxime chloride
equivalent to 476.6 mg of pralidoxime

Usual dosage: See insert

Store at 25°C (77°F). Excursions
permitted to 15-30°C (59-86°F).

Keep from freezing.

Protect from light.

Manufactured By/Distributed By
Meridian Medical Technologies®, LLC
St. Louis, MO 63146
0002197

NDC 11704 62001

Principal Display Panel - DuoDote Syringe Label

Rx Only

NDC 11704 62001

Do not
place fingers
on green tip
(needled end)

Usual dosage:
See insert.

DuoDote®

(atropine and pralidoxime
chloride injection)

Single-Dose Auto-Injector

Delivers an intramuscular injection
of 2.1 mg/0.7 mL of atropine
600 mg/2 mL (300 mg/mL) of pralidoxime
chloride equivalent to 476.6 mg of pralidoxime

For use in
Nerve Agent or
Insecticide Poisoning

For adults and pediatric
patients weighing
41 kg +
or 90 lb +

For product inquiry call 1-833-739-0945

Manufactured By/Distributed By
Meridian Medical Technologies®, LLC
St. Louis, MO 63146
©2020 Meridian Medical Technologies